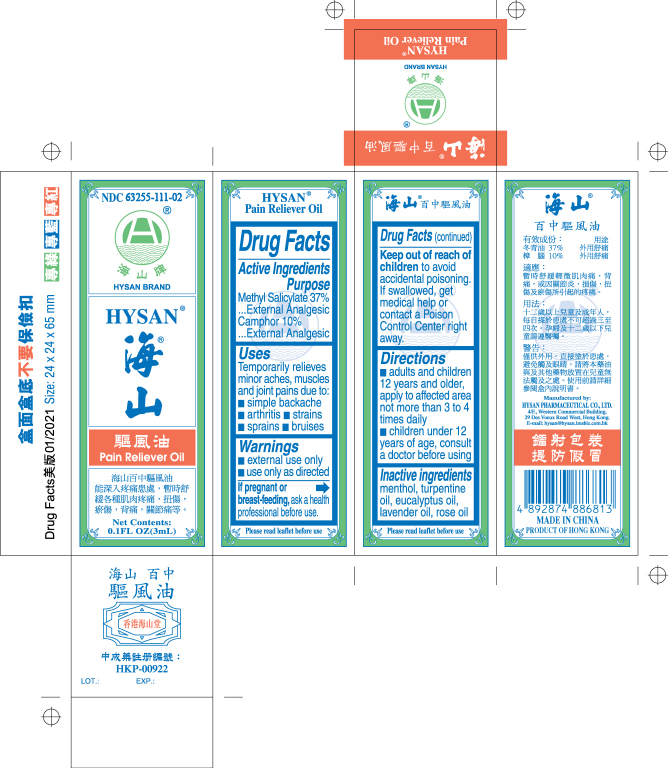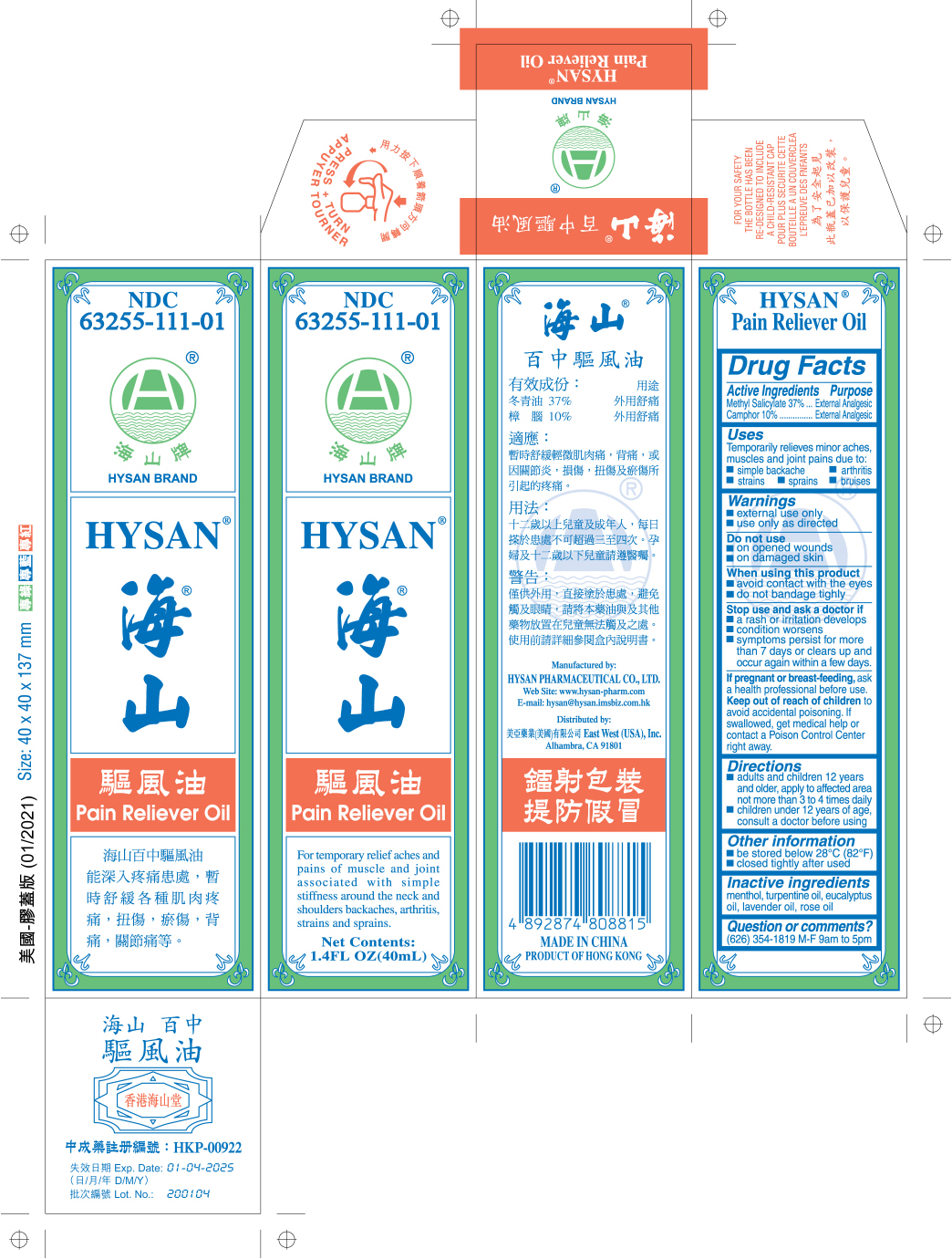 DRUG LABEL: HYSAN PAIN RELIEVER
NDC: 63255-111 | Form: OIL
Manufacturer: HYSAN PHARMACEUTICAL CO LTD
Category: otc | Type: HUMAN OTC DRUG LABEL
Date: 20241007

ACTIVE INGREDIENTS: METHYL SALICYLATE 37 g/100 mL; CAMPHOR (SYNTHETIC) 10 g/100 mL
INACTIVE INGREDIENTS: MENTHOL; TURPENTINE OIL; EUCALYPTUS OIL; LAVENDER OIL; ROSE OIL

Drug Facts

Active Ingredients

Methyl Salicylate 37%

Camphor 10%

Purpose

External Analgesic

Uses

Temporarily relieves minor aches, muscles and joint pains due to:

- simple backache
- arthritis
- strains
- sprains
- bruises

warnings

- external use only
- use only as directed

Do not use

- on opened wound
- on damaged skin

When using this product

- avoid contact with the eyes
- do not bandage tighly

Stop use and ask a doctor if

- a rash or irritation develops
- condition worsens
- symptoms persist for more than 7 days or clears up and occur again within a few days

PREGNANCY OR BREAST FEEDING

if pregnant or breast-feeding, ask a health professional before use

Keep out of reach of children to avoid accidental poisoning. If swallowed, get medical help or contact a Poison Control Center right away

Directions

- adults and children 12 years and older, apply to affected area not more than 3 to 4 times daily
- children under 12 years of age, consult a doctor before using

Other information

- be stored below 28°C (82°F)
- closed tightly after used

Inactive ingredients

menthol, turpentine oil, eucalyptus oil, lavender oil, rose oil

QUESTIONS

Question or comments?

(626) 354 1819 M-F 9am to 5pm